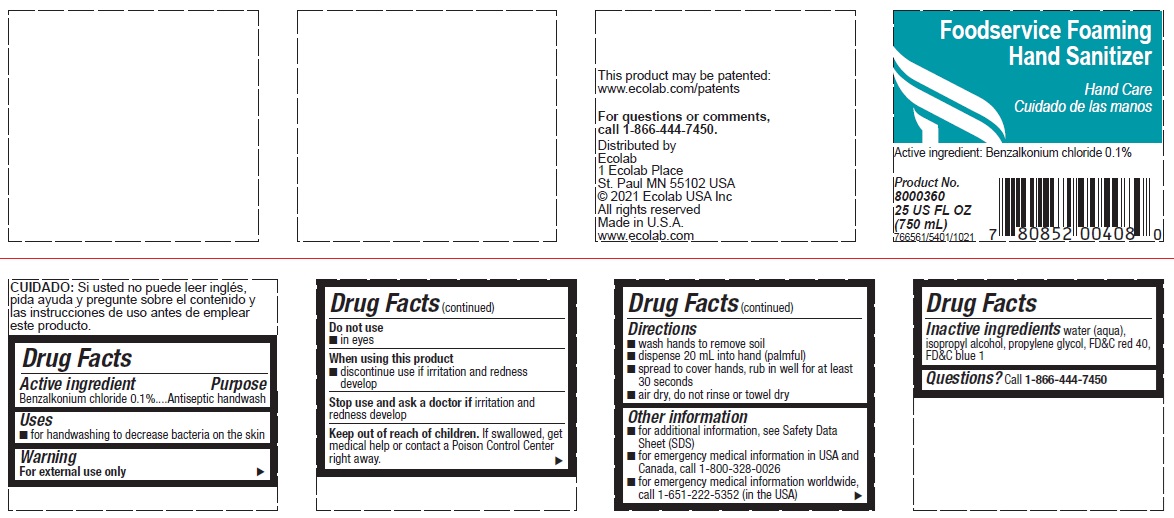 DRUG LABEL: PureForce
NDC: 47593-567 | Form: SOLUTION
Manufacturer: Ecolab Inc.
Category: otc | Type: HUMAN OTC DRUG LABEL
Date: 20251230

ACTIVE INGREDIENTS: BENZALKONIUM CHLORIDE 1 mg/1 mL
INACTIVE INGREDIENTS: WATER; ISOPROPYL ALCOHOL; PROPYLENE GLYCOL; FD&C RED NO. 40; FD&C BLUE NO. 1

Drug Facts

Active ingredient

Benzalkonium chloride, 0.1%

Purpose

Antiseptic handwash

Uses

- For handwashing to decrease bacteria on the skin

Warnings

For external use only

Do not use

- In eyes

When using this product

- Discontinue use if irritation and redness develop

Stop use and ask a doctor if skin irritation and redness develop

Keep out of reach of children. If swallowed, get medical help or contact a Poison Control Center right away.

Directions

- Wash hands to remove soil
- dispense 20 mL into hand (palmful)
- spread to cover hands, rub in well for at least 30 seconds
- air dry, do not rinse or towel dry

Other information

- for additional information, see Safety Data Sheet (SDS)
- for emergency medical information in USA and Canada, call 1-800-328-0026
- for emergency medical information worldwide, call 1-651-222-5352 (in the USA)

INACTIVE INGREDIENT

Inactive ingredients water (aqua), isopropyl alcohol, propylene glycol, FD&C red 40, FD&C blue 1

Questions? call 1-866-444-7450

Principal Display Panel and Representative Label

Foodservice Foaming

Hand Sanitizer

Hand Care

Active ingredient: Benzalkonium Chloride 0.1%

Product No.

8000360

25 US FL OZ

(750 mL)

766561/5401/1021

For questions or comments,

call 1-866-444-7450.

Distributed by
Ecolab

1 Ecolab Place

St Paul MN 55102 USA

© 2021 Ecolab USA Inc

All rights reserved

Made in U.S.A.